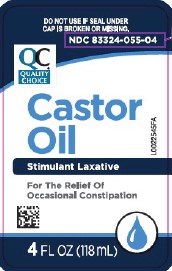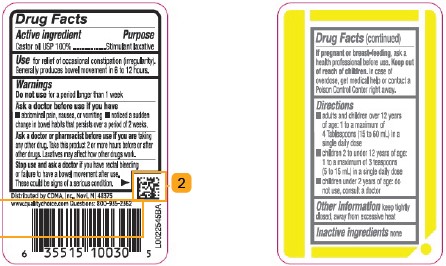 DRUG LABEL: Castor Oil
NDC: 83324-055 | Form: LIQUID
Manufacturer: Chain Drug Marketing Association
Category: otc | Type: HUMAN OTC DRUG LABEL
Date: 20260223

ACTIVE INGREDIENTS: CASTOR OIL 1 g/1 mL

Quality Choice 078.000/078AA
Castor Oil

Active ingredients

Castor oil USP 100%

Purpose

Stimulant laxative

Use

for relief of occasional constipation (irregularity). Generally produces bowel movement in 6 to 12 hours.

Warnings

for this product

Do not use

for a period longer than 1 week

Ask a doctor before use if you have

- abdominal pain, nausea, or vomiting
- noticed a sudden change in bowel habits that persists over a period of 2 weeks

Ask a doctor or pharmacist before use if you are

taking any other drug. Take this product 2 or more hours before or after other drugs. Laxatives may affect how other drugs work.

Stop use and ask a doctor if

you have rectal bleeding or failure to have a bowel movement after use. These could be signs of a serious condition.

If pregnant or breast-feeding,

ask a health professional before use.

Keep out of reach of children.

In case of overdose, get medical help or contact a Poison Control Center right away.

Directions

- adults and children over 12 years of age: 1 to a maximum of 4 Tablespoons (15 to 60 mL) in a single daily dose
- children 2 to under 12 years of age: 1 to a maximum of 3 teaspoons (5 to 15 mL) in a single daily dose
- children under 2 years of age: do not use, consult a doctor

Other information

keep tightly closed, away from excessive heat

Inactive ingredients

None

Adverse Reaction

Distributed by CDMA, Inc., Novi, MI 48375

www.qualitychoice.com Questions: 800-935-2362

Principal Display Panel

DO NOT USE IF SEAL UNDER CAP IS BROKEN OR MISSING.

NDC 83324-055-04

QC®

Quality Choice

Castor Oil

Stimulant Laxative

For the relief of occasional constipation

4 FL OZ (118 mL)